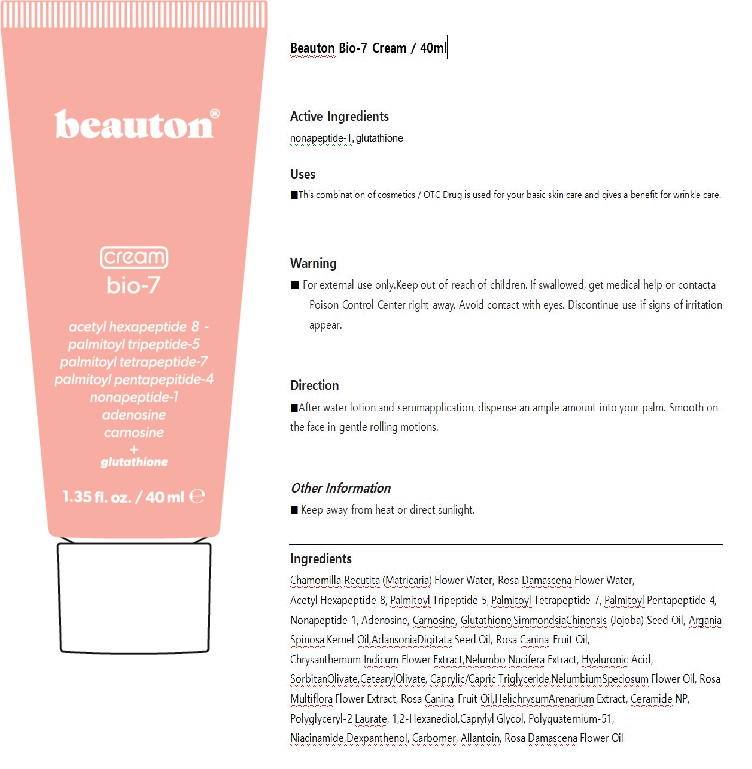 DRUG LABEL: Bio-7
NDC: 71583-1003 | Form: CREAM
Manufacturer: B.N.Trinity Co.,Ltd
Category: otc | Type: HUMAN OTC DRUG LABEL
Date: 20200522

ACTIVE INGREDIENTS: NONAPEPTIDE-1 2 g/100 mL; GLUTATHIONE 3.26 g/100 mL
INACTIVE INGREDIENTS: CARNOSINE; ADENOSINE; NIACINAMIDE

Drug Facts

ACTIVE INGREDIENT

nonapeptide-1, glutathione

PURPOSE

■This combination of cosmetics / OTC Drug is used for your basic skin care and gives a benefit for wrinkle care.

KEEP OUT OF REACH OF THE CHILDREN

WARNINGS

■ For external use only.Keep out of reach of children. If swallowed, get medical help or contacta Poison Control Center right away. Avoid contact with eyes. Discontinue use if signs of irritation appear

DOSAGE AND ADMINISTRATION

for external use only

INACTIVE INGREDIENT

Chamomilla Recutita (Matricaria) Flower Water, Acetyl Hexapeptide-8, Palmitoyl Tripeptide-5, Palmitoyl Tetrapeptide-7, Palmitoyl Pentapeptide-4, Nonapeptide-1, Adenosine, Carnosine, Glutathione, Glycine Soja (Soybean) Phytoplacenta Extract, Hyaluronic Acid, Chrysanthemum,Indicum Flower Extract,Nelumbo Nucifera Extract, Rosa Multiflora Flower Extract,

HelichrysumArenarium Extract,SclerocaryaBirrea Seed Oil, Caprylic/Capric Triglyceride, Polyglyceryl-2 Laurate, Rosa Canina Fruit Oil,NelumbiumSpeciosum Flower Oil, Ceramide NP, Carbomer, Polyquaternium-51, Niacinamide,Dexpanthenol, Allantoin, 1,2-Hexanediol,

Caprylyl Glycol, Citrus Aurantium Amara (Bitter Orange) Flower Oil

INDICATIONS AND USAGE

■After water lotion application, dispense an ample amount into your palm. Smooth on the face in gentle rolling motions.